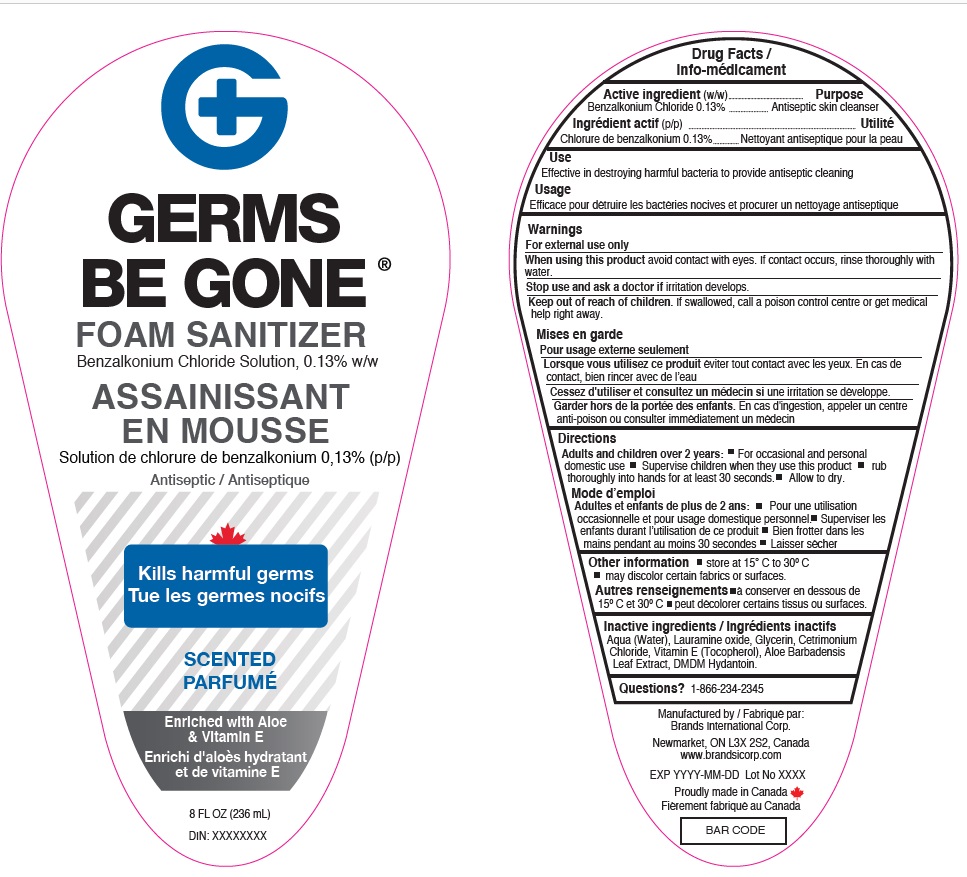 DRUG LABEL: Germs be gone Sanitizer
NDC: 50157-526 | Form: SOLUTION
Manufacturer: Brands International Corporation
Category: otc | Type: HUMAN OTC DRUG LABEL
Date: 20210814

ACTIVE INGREDIENTS: BENZALKONIUM CHLORIDE 0.13 g/100 mL
INACTIVE INGREDIENTS: GLYCERIN; WATER; ALOE; CETRIMONIUM CHLORIDE; DMDM HYDANTOIN; LAURAMINE OXIDE

Germs be Gone Foam sanitizer - Scented

Active Ingredient(s)

Benzalkonium Chloride 0.13% v/v. Purpose: Antiseptic

Purpose

Antiseptic skin cleanser

Use

Effective in destroying harmful bacteria to provide antiseptic cleaning

Warnings

For external use only. Flammable. Keep away from heat or flame

Do not use

- in children less than 2 months of age
- on open skin wounds

When using this product keep out of eyes, ears, and mouth. In case of contact with eyes, rinse eyes thoroughly with water.
Stop use and ask a doctor if irritation or rash occurs. These may be signs of a serious condition.
Keep out of reach of children. If swallowed, get medical help or contact a Poison Control Center right away.

Stop use and ask a doctor if irritation or rash occurs. These may be signs of a serious condition.

Keep out of reach of children. If swallowed, get medical help or contact a Poison Control Center right away.

Directions

Adults and children over 2 years: For occasional and personal domestic use Supervise children when they use this product rub
thoroughly into hands for at least 30 seconds. Allow to dry.

Other information

Store between 15-30C (59-86F). Avoid freezing and excessive heat above 40C (104F)

may discolor certain fabrics or surfaces.

Inactive ingredients

Aqua (Water), Lauramine oxide, Glycerin, Cetrimonium Chloride, Vitamin E (Tocopherol), Aloe Barbadensis Leaf Extract, DMDM Hydantoin